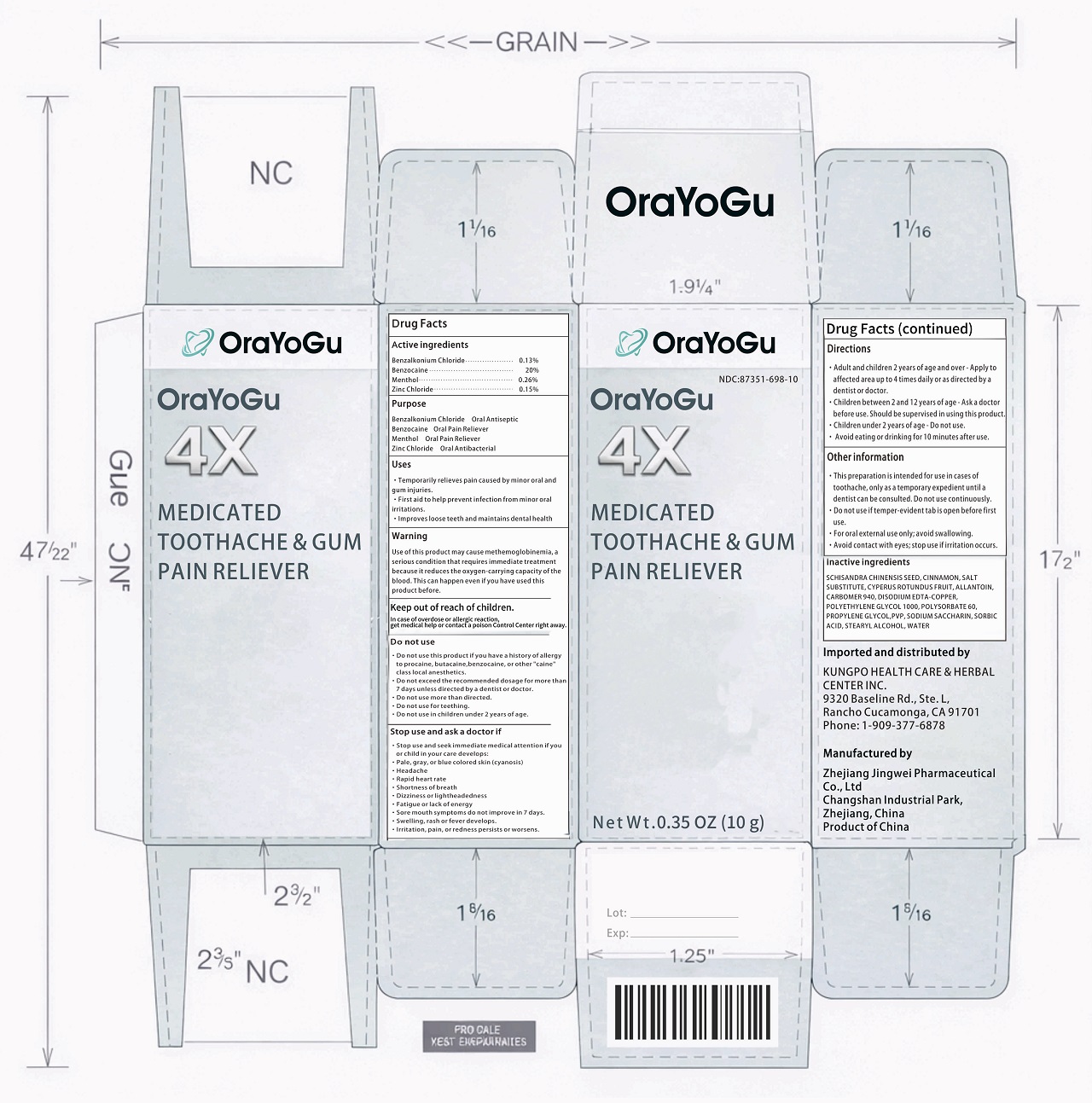 DRUG LABEL: Ora YoGu 4X Medicated Tooth and Gum Pain Reliever
NDC: 87351-698 | Form: LIQUID
Manufacturer: Kungpo Health Care & Herbal Center Inc
Category: otc | Type: HUMAN OTC DRUG LABEL
Date: 20260122

ACTIVE INGREDIENTS: BENZALKONIUM CHLORIDE 0.13 g/100 mL; BENZOCAINE 20 g/100 mL; MENTHOL 0.26 g/100 mL; ZINC CHLORIDE 0.15 g/100 mL
INACTIVE INGREDIENTS: SCHISANDRA CHINENSIS SEED; CINNAMON; SALT SUBSTITUTE; CYPERUS ROTUNDUS FRUIT; ALLANTOIN; CARBOMER 940; DISODIUM EDTA-COPPER; POLYETHYLENE GLYCOL 1000; POLYSORBATE 60; PROPYLENE GLYCOL; PVP; SODIUM SACCHARIN; SORBIC ACID; STEARYL ALCOHOL; WATER

DRUG FACTS

Active ingredients

Benzalkonium Chloride 0.13%
Benzocaine 20%
Menthol 0.26%
Zinc Chloride 0.15%

Purpose

Benzalkonium Chloride Oral Antibacterial
Benzocaine Oral Antibacterial
Menthol Oral Antibacterial
Zinc Chloride Oral Antibacterial

Uses

- Temporarily relieves pain caused by minor oral and gum injuries.
- First aid to help prevent infection from minor oral irritations.
- Improves loose teeth and maintains dental health.

Warning

Use of this product may cause methemoglobinemia, a serious condition that requires immediate treatment because it reduces the oxygen-carrying capacity of the blood. This can happen even if you have used this product before.

- Do not use this product if you have a history of allergy to procaine, butacaine, benzocaine, or other "caine" class local anesthetics.
- Do not exceed the recommended dosage for more than 7 days unless directed by a dentist or doctor.

Stop use and ask a doctor if

- Stop use and seek immediate medical attention if you or child in your care develops:
- Pale, gray, or blue colored skin (cyanosis)
- Headache
- Rapid heart rate
- Shortness of breath
- Dizziness or lightheadedness
- Fatigue or lack of energy
- Sore mouth symptoms do not improve in 7 days.
- Swelling, rash or fever develops.
- Irritation, pain, or redness persists or worsens.

Keep out of reach of children.

In case of overdose or allergic reaction, get medical help or contact a poison Control Center right away.

Directions

- Adult and children 2 years of age and over - Apply to affected area up to 4 times daily or as directed by a dentist or doctor.
- Children between 2 and 12 years of age - Ask a doctor before use. Should be supervised in using this product.
- Children under 2 years of age - Do not use.

Other information

- This preparation is intended for use in cases of toothache, only as a temporary expedient until a dentist can be consulted. Do not use continuously.
- Do not use if temper-evident tab is open before first use.

Inactive ingredients

SCHISANDRA CHINENSIS SEED, CINNAMON, SALT SUBSTITUTE, CYPERUS ROTUNDUS FRUIT, ALLANTOIN, CARBOMER 940, DISODIUM EDTA-COPPER, POLYETHYLENE GLYCOL 1000, POLYSORBATE 60, PROPYLENE GLYCOL, PVP, SODIUM SACCHARIN, SORBIC ACID, STEARYL ALCOHOL, WATER

Manufactured by

Zhejiang Jingwei Pharmaceutical Co., Ltd
Changshan Industrial Park, Zhejiang, China
Product of China

Imported and distributed by

KUNGPO HEALTH CARE & HERBAL CENTER INC.
9320 Baseline Rd., Ste. L，
Rancho Cucamonga, CA 91701
Phone: 909-377-6878